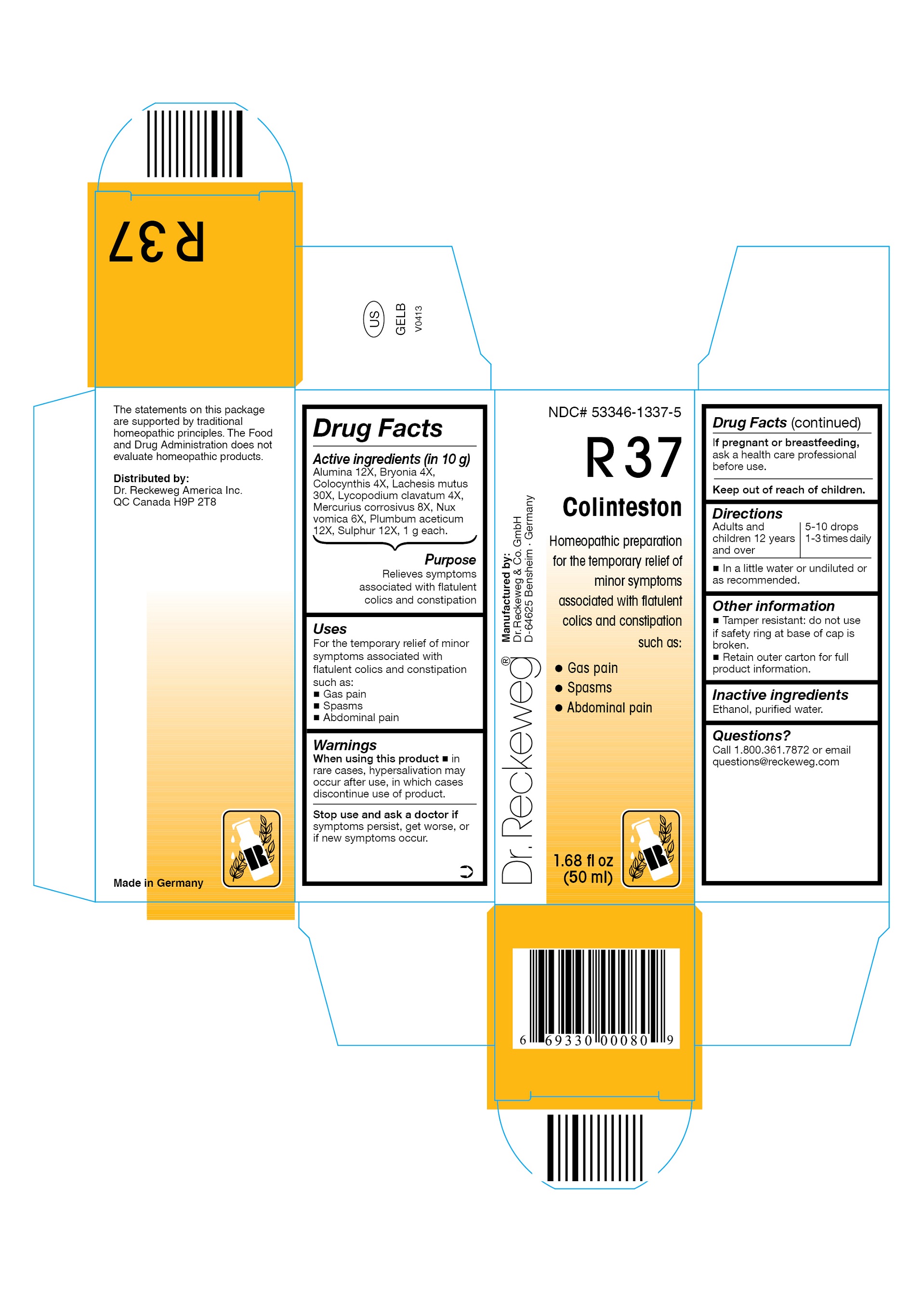 DRUG LABEL: DR. RECKEWEG R37 Colinteston
NDC: 53346-1337 | Form: LIQUID
Manufacturer: PHARMAZEUTISCHE FABRIK DR. RECKEWEG & CO
Category: homeopathic | Type: HUMAN OTC DRUG LABEL
Date: 20130408

ACTIVE INGREDIENTS: ALUMINUM OXIDE 12 [hp_X]/50 mL; BRYONIA DIOICA ROOT 4 [hp_X]/50 mL; CITRULLUS COLOCYNTHIS FRUIT PULP 4 [hp_X]/50 mL; LACHESIS MUTA VENOM 30 [hp_X]/50 mL; LYCOPODIUM CLAVATUM SPORE 4 [hp_X]/50 mL; MERCURIC CHLORIDE 8 [hp_X]/50 mL; STRYCHNOS NUX-VOMICA SEED 6 [hp_X]/50 mL; LEAD ACETATE 12 [hp_X]/50 mL; SULFUR 12 [hp_X]/50 mL
INACTIVE INGREDIENTS: ALCOHOL; WATER

DR. RECKEWEG R37 Colinteston

Active ingredients
Alumina 12X, Bryonia 4X, Colocynthis 4X, Lachesis mutus 30X, Lycopodium clavatum 4X, Mercurius corrosivus 8X, Nux vomica 6X, Plumbum aceticum 12X, Sulphur 12X, 1 g each in 10 g.

Purpose
Relieves symptoms associated with flatulent colics and constipation

Uses
For the temporary relief of minor symptoms associated with flatulent colics and constipation such as:

- Gas pain
- Spasms
- Abdominal pain

Warnings

When using this product

- in rare cases, hypersalivation may occur after use, in which cases discontinue use of product.

Stop use and ask a doctor if symptoms persist, get worse, or if new symptoms occur.

PREGNANCY OR BREAST FEEDING

If pregnant or breastfeeding, ask a health care professional before use.

Keep out of reach of children.

Directions
Adults and children ≥ 12 years 5-10 drops 1-3 times daily in a little water or undiluted or as recommended.

Other information

- Tamper resistant: do not use if safety ring at base of cap is broken.
- Retain outer carton for full product information.

Inactive ingredients
Ethanol, purified water.

Questions?
Call 1-800-361-7872 or email questions@reckeweg.com

PACKAGE LABEL

NDC# 53346-1337-5
Dr. Reckeweg R37 Colinteston
Homeopathic preparation for the temporary relief of minor symptoms associated with flatulent colics and constipation such as:

- Gas pain
- Spasms
- Abdominal pain

Manufactured by:
Dr. Reckeweg Co. GmbH
D-64625 Bensheim
Germany
1.68 fl oz
(50 ml)